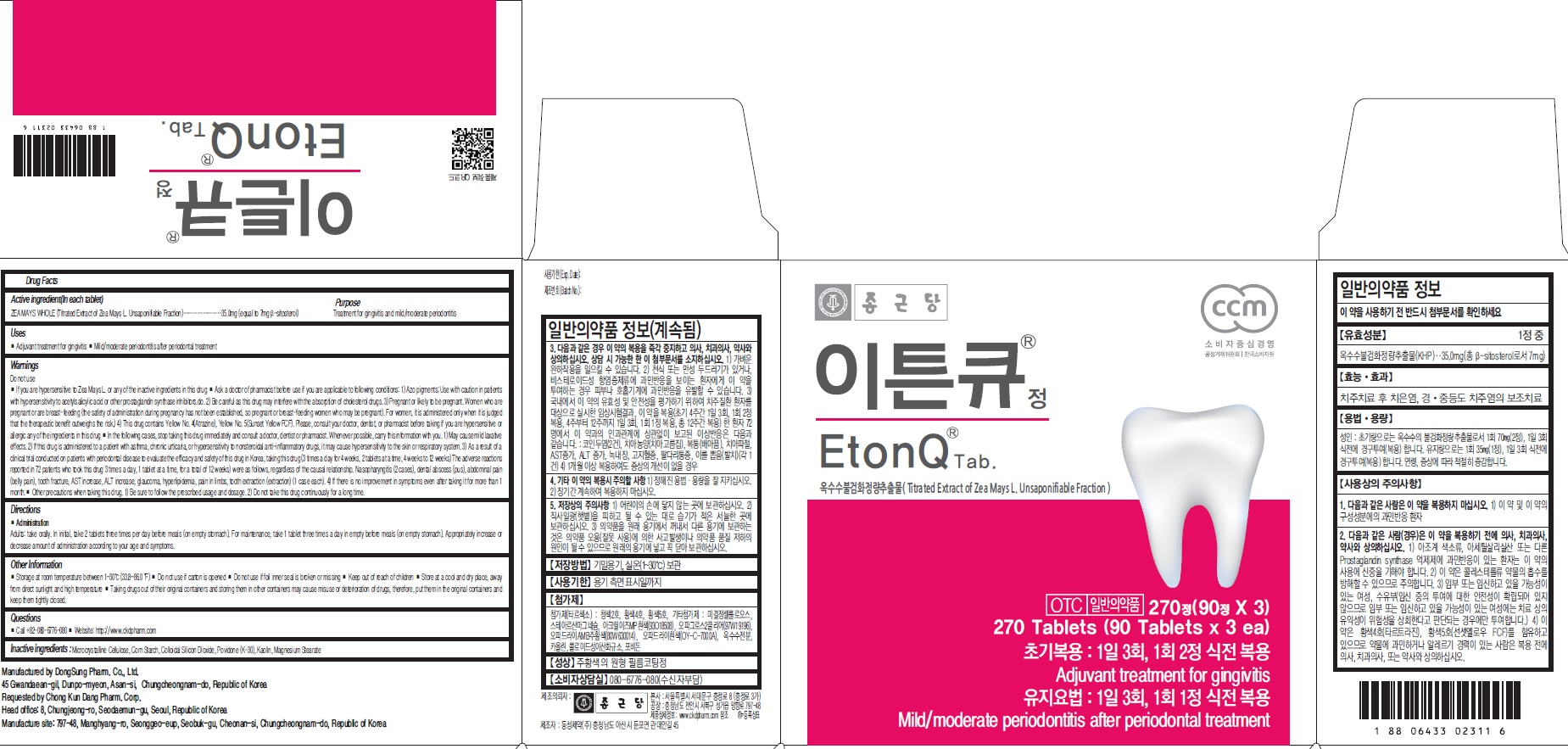 DRUG LABEL: Eton Q
NDC: 82024-010 | Form: TABLET
Manufacturer: Chong Kun Dang Pharm. Corp.
Category: otc | Type: HUMAN OTC DRUG LABEL
Date: 20210712

ACTIVE INGREDIENTS: ZEA MAYS WHOLE 35.0 mg/1 1
INACTIVE INGREDIENTS: MICROCRYSTALLINE CELLULOSE; STARCH, CORN; SILICON DIOXIDE; Povidone; Kaolin; Magnesium Stearate

ACTIVE INGREDIENT

Active ingredient (In each tablet)
ZEA MAYS WHOLE (Titrated Extract of Zea Mays L. Unsaponifiable Fraction)………………35.0mg (equal to 7mg β-sitosterol)

INACTIVE INGREDIENTS

Microcrystalline Cellulose, Corn Starch, Colloidal Silicon Dioxide, Povidone (K-30), Kaolin, Magnesium Stearate

PURPOSE

Treatment for gingivitis and mild/moderate periodontitis

WARNINGS

Do not use
■ If you are hypersensitive to Zea Mays L. or any of the inactive ingredients in this drug ■ Ask a doctor of pharmacist before use if you are applicable to following conditions: 1) Azo pigments; Use with caution in patients with hypersensitivity to acetylsalicylic acid or other prostaglandin synthase inhibitors.do. 2) Be careful as this drug may interfere with the absorption of cholesterol drugs. 3) Pregnant or likely to be pregnant. Women who are pregnant or are breast-feeding (the safety of administration during pregnancy has not been established, so pregnant or breast-feeding women who may be pregnant). For women, it is administered only when it is judged that the therapeutic benefit outweighs the risk.) 4) This drug contains Yellow No. 4(Atrazine), Yellow No. 5(Sunset Yellow FCF). Please, consult your doctor, dentist, or pharmacist before taking if you are hypersensitive or allergic any of the ingredients in this drug ■ In the following cases, stop taking this drug immediately and consult a doctor, dentist or pharmacist. Whenever possible, carry this information with you. 1) May cause mild laxative effects. 2) If this drug is administered to a patient with asthma, chronic urticaria, or hypersensitivity to nonsteroidal anti-inflammatory drugs, it may cause hypersensitivity to the skin or respiratory system. 3) As a result of a clinical trial conducted on patients with periodontal disease to evaluate the efficacy and safety of this drug in Korea, taking this drug (3 times a day for 4 weeks, 2 tablets at a time, 4 weeks to 12 weeks) The adverse reactions reported in 72 patients who took this drug 3 times a day, 1 tablet at a time, for a total of 12 weeks) were as follows, regardless of the causal relationship. Nasopharyngitis (2 cases), dental abscess (pus), abdominal pain (belly pain), tooth fracture, AST increase, ALT increase, glaucoma, hyperlipidemia, pain in limbs, tooth extraction (extraction) (1 case each). 4) If there is no improvement in symptoms even after taking it for more than 1 month.■ Other precautions when taking this drug. 1) Be sure to follow the prescribed usage and dosage. 2) Do not take this drug continuously for a long time.

KEEP OUT OF REACH OF CHILDREN

NA

Uses

■ Adjuvant treatment for gingivitis
■ Mild/moderate periodontitis after periodontal treatment

Directions

■ Administration
Adults: take orally. In initial, take 2 tablets three times per day before meals (on empty stomach). For maintenance, take 1 tablet three times a day in empty before meals (on empty stomach). Appropriately increase or decrease amount of administration according to your age and symptoms.

Other Information

■ Storage at room temperature between 1~30℃ (33.8~86.0 °F) ■ Do not use if carton is opened ■ Do not use if foil inner seal is broken or missing ■ Keep out of reach of children ■ Store at a cool and dry place, away from direct sunlight and high temperature ■ Taking drugs out of their original containers and storing them in other containers may cause misuse or deterioration of drugs, therefore, put them in the original containers and keep them tightly closed.

QUESTIONS

■ Call +82-080-6776-080 ■ Website: http://www.ckdpharm.com